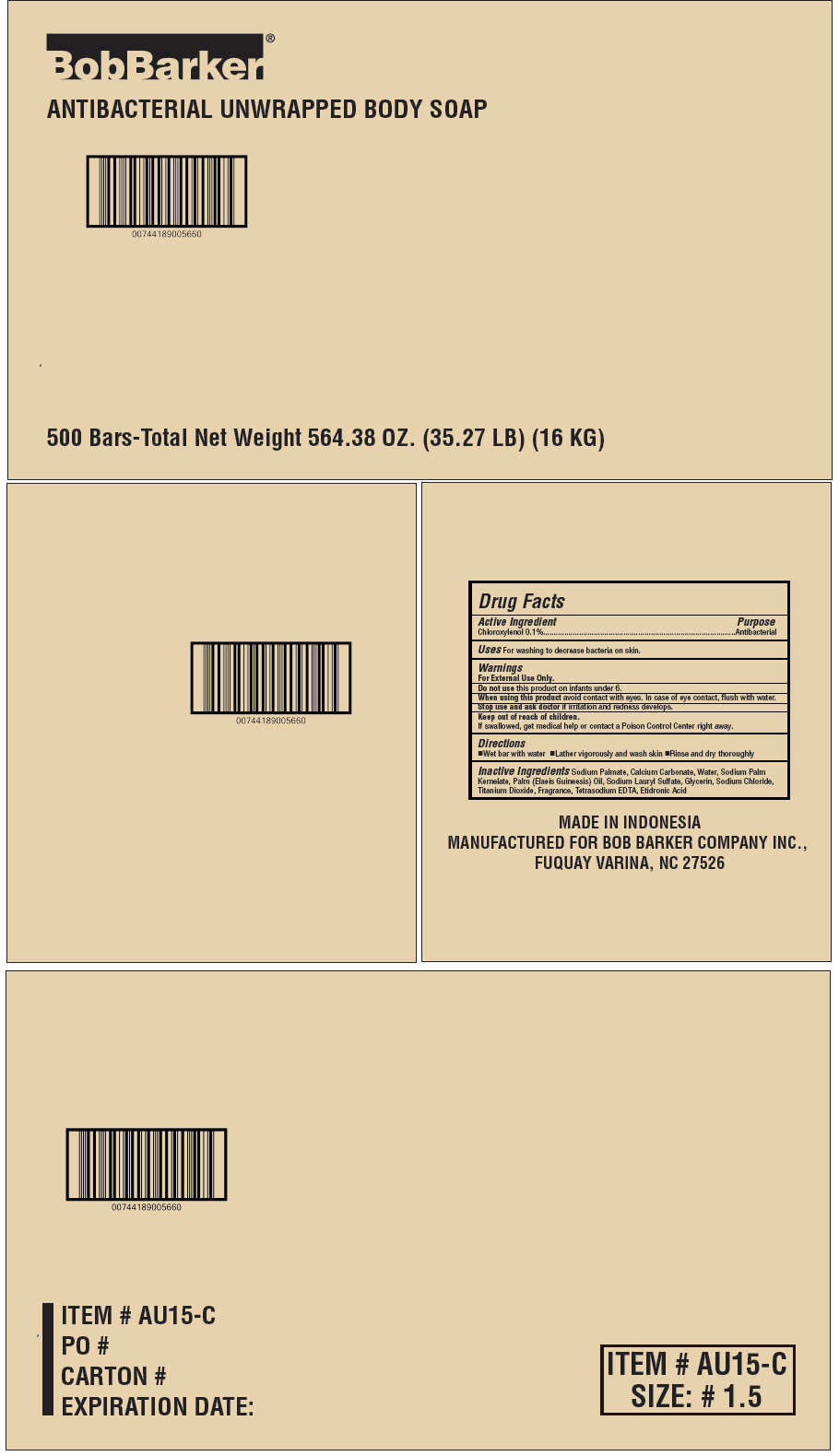 DRUG LABEL: Bob Barker Antibacterial unwrapped body
NDC: 53247-116 | Form: SOAP
Manufacturer: Bob Barker Company Inc.
Category: otc | Type: HUMAN OTC DRUG LABEL
Date: 20190930

ACTIVE INGREDIENTS: CHLOROXYLENOL 0.1 g/100 g
INACTIVE INGREDIENTS: Sodium Palmate; Calcium Carbonate; Water; Sodium Palm Kernelate; PALM OIL; Glycerin; Sodium Chloride; Titanium Dioxide; Edetate Sodium; Etidronic Acid

Bob Barker® Antibacterial unwrapped body soap

Drug Facts

Active Ingredient

Chloroxylenol 0.1%

Purpose

Antibacterial

Uses

For washing to decrease bacteria on skin.

Warnings

For External Use Only.

Do not use this product on infants under 6.

When using this product avoid contact with eyes. In case of eye contact, flush with water.

Stop use and ask doctor if irritation and redness develops.

Keep out of reach of children.
If swallowed, get medical help or contact a Poison Control Center right away.

Directions

- Wet bar with water
- Lather vigorously and wash skin
- Rinse and dry thoroughly

Inactive Ingredients

Sodium Palmate, Calcium Carbonate, Water, Sodium Palm Kernelate, Palm (Elaeis Guineesis) Oil, Sodium Lauryl Sulfate, Glycerin, Sodium Chloride, Titanium Dioxide, Fragrance, Tetrasodium EDTA, Etidronic Acid

PRINCIPAL DISPLAY PANEL - 500 Bar Case

BobBarker®

ANTIBACTERIAL UNWRAPPED BODY SOAP

500 Bars-Total Net Weight 564.38 OZ. (35.27 LB) (16 KG)